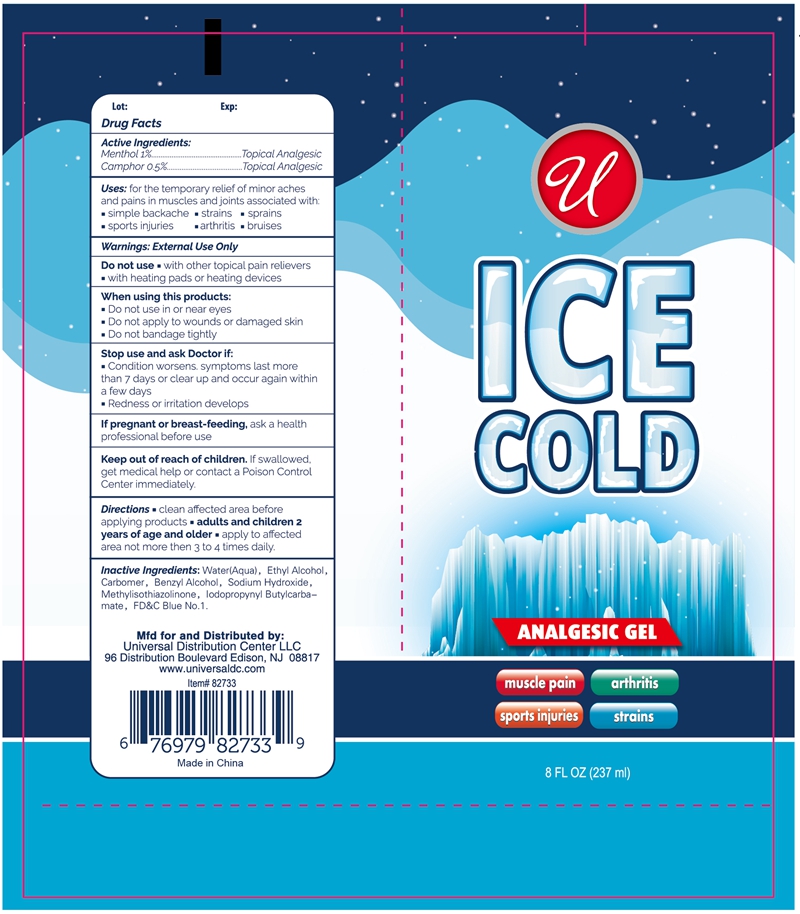 DRUG LABEL: U ICE COLD
NDC: 52000-045 | Form: OINTMENT
Manufacturer: UNIVERSAL DISTRIBUTION CENTER LLC
Category: otc | Type: HUMAN OTC DRUG LABEL
Date: 20230901

ACTIVE INGREDIENTS: CAMPHOR, (-)- 0.5 g/100 g; MENTHOL 1 g/100 g
INACTIVE INGREDIENTS: FD&C BLUE NO. 1; WATER; BENZYL ALCOHOL; CARBOMER 934; METHYLISOTHIAZOLINONE; IODOPROPYNYL BUTYLCARBAMATE; ISOPROPYL ALCOHOL; SODIUM HYDROXIDE

Drug Facts Active Ingredients:

Menthol 1 percent...............................................Topical Analgesic

Camphor 0.5 percent.........................................Topical Analgesic

Purpose

Topical Analgesic

Uses:

for the temporary relief of minor aches and pains in muscles and joints associated with:

simple backache, strains, sprains, sports injuries, arthritis, bruises

Warnings: External Use Only

For external use only.

Do not use

with other topical pain relievers

with heating pads or heating devices

When using this product:

- Do not use in or near eyes
- Do not apply to wounds or damaged skin
- Do not bandage tightly

Stop use and ask Doctor if:

- Condition worsens, symptoms last more than 7 days or clear up and occur again within a few days
- Redness or irritation develops

If pregnant or breast-feeding,

ask a health professional before use

Keep out of reach of children.

If swallowed, get medical help or contact a Posion Control Center immediately.

Directions

- clean affected area before applying products
- adults and children 2 years of age and older
- apply to affected area not more than 3 to 4 times daily